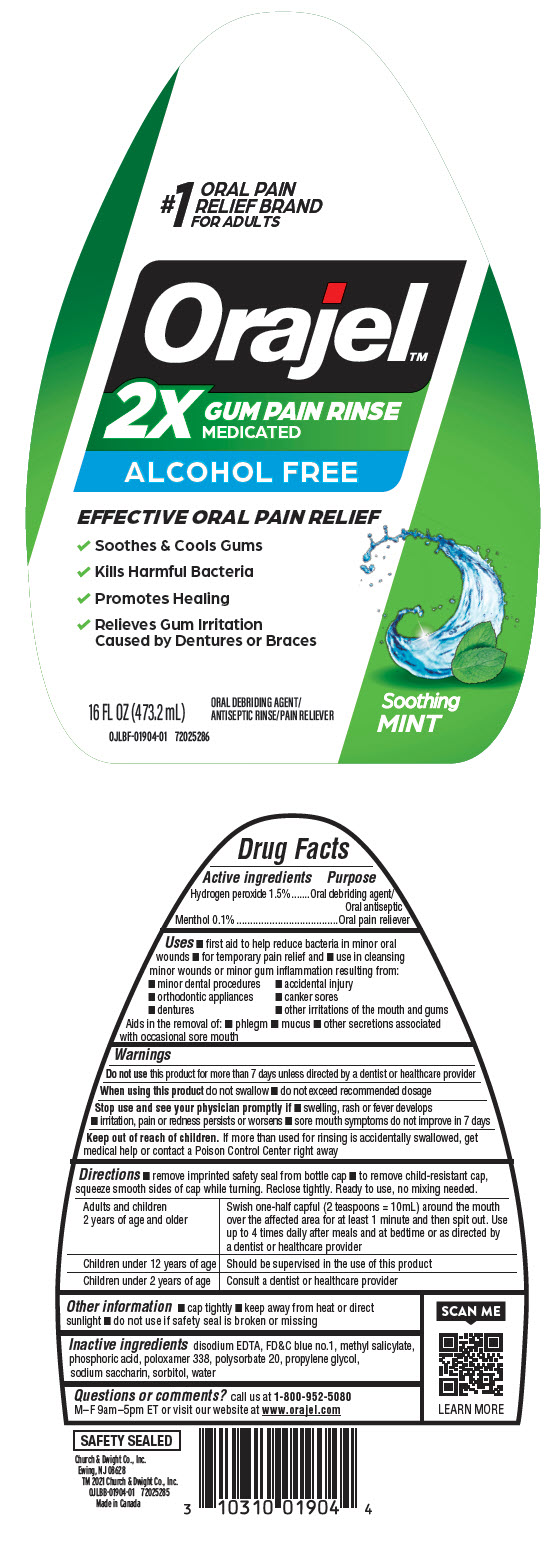 DRUG LABEL: Orajel 2x Gum Pain 

NDC: 10237-799 | Form: RINSE
Manufacturer: Church & Dwight Co., Inc.
Category: otc | Type: HUMAN OTC DRUG LABEL
Date: 20241127

ACTIVE INGREDIENTS: MENTHOL, UNSPECIFIED FORM 1 mg/1 mL; HYDROGEN PEROXIDE 15 mg/1 mL
INACTIVE INGREDIENTS: EDETATE DISODIUM ANHYDROUS; FD&C BLUE NO. 1; METHYL SALICYLATE; PHOSPHORIC ACID; POLOXAMER 338; POLYSORBATE 20; PROPYLENE GLYCOL; SACCHARIN SODIUM; SORBITOL; WATER

Orajel™2x Gum Pain Rinse
Alcohol-Free

Drug Facts

ACTIVE INGREDIENT

Active ingredients | Purpose
Hydrogen peroxide 1.5% | Oral debriding agent/Oral antiseptic
Menthol 0.1% | Oral pain reliever

Uses

- first aid to help reduce bacteria in minor oral wounds
- for temporary pain relief and
- use in cleansing minor wounds or minor gum inflammation resulting from:
  - minor dental procedures
  - accidental injury
  - orthodontic appliances
  - canker sores
  - dentures
  - other irritations of the mouth and gums

Aids in the removal of:

- phlegm
- mucus
- other secretions associated with occasional sore mouth

Warnings

DO NOT USE

Do not usethis product for more than 7 days unless directed by a dentist or healthcare provider

When using this productdo not swallow

- do not exceed recommended dosage

Stop use and see your physician promptly if

- swelling, rash or fever develops
- irritation, pain or redness persists or worsens
- sore mouth symptoms do not improve in 7 days

Keep out of reach of children.If more than used for rinsing is accidentally swallowed, get medical help or contact a Poison Control Center right away

Directions

- remove imprinted safety seal from bottle cap
- to remove child-resistant cap, squeeze smooth sides of cap while turning. Reclose tightly. Ready to use, no mixing needed.

Adults and children 2 years of age and older | Swish one-half capful (2 teaspoons = 10mL) around the mouth over the affected area for at least 1 minute and then spit out. Use up to 4 times daily after meals and at bedtime or as directed by a dentist or healthcare provider
Children under 12 years of age | Should be supervised in the use of this product
Children under 2 years of age | Consult a dentist or healthcare provider

Other information

- cap tightly
- keep away from heat or direct sunlight
- do not use if safety seal is broken or missing

Inactive ingredients

disodium EDTA, FD&C blue no.1, methyl salicylate, phosphoric acid, poloxamer 338, polysorbate 20, propylene glycol, sodium saccharin, sorbitol, water

Questions or comments?

call us at 1-800-952-5080M–F 9am–5pm ET or visit our website at www.orajel.com

PRINCIPAL DISPLAY PANEL - 473.2 mL Bottle Label

1#
ORAL PAIN
RELIEF BRAND
FOR ADULTS

Orajel™
2X
GUM PAIN RINSE
MEDICATED
ALCOHOL FREE

EFFECTIVE ORAL PAIN RELIEF

- Soothes & Cools Gums
- Kills Harmful Bacteria
- Promotes Healing
- Relieves Gum Irritation
  Caused by Dentures or Braces

ORAL DEBRIDING AGENT/
ANTISEPTIC RINSE/PAIN RELIEVER

Soothing
MINT

16 FL OZ (473.2 mL)

OJLBF-01904-01 72025286